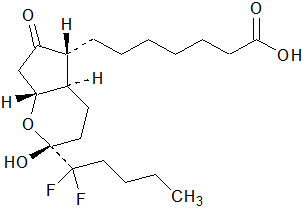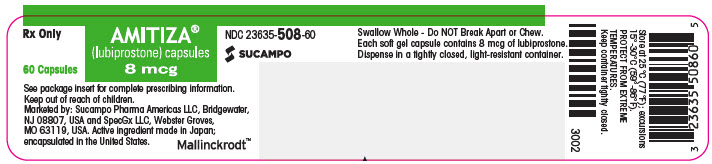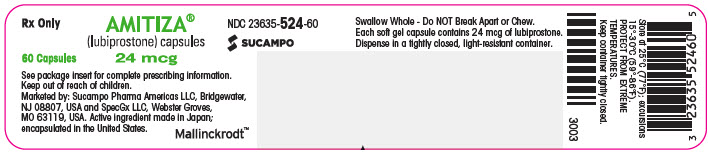 DRUG LABEL: Amitiza
NDC: 23635-508 | Form: CAPSULE, GELATIN COATED
Manufacturer: SpecGx LLC
Category: prescription | Type: HUMAN PRESCRIPTION DRUG LABEL
Date: 20250911

ACTIVE INGREDIENTS: LUBIPROSTONE 8 ug/1 1
INACTIVE INGREDIENTS: MEDIUM-CHAIN TRIGLYCERIDES; GELATIN, UNSPECIFIED; SORBITOL; FERRIC OXIDE RED; TITANIUM DIOXIDE; WATER

HIGHLIGHTS OF PRESCRIBING INFORMATION

These highlights do not include all the information needed to use AMITIZA safely and effectively. See full prescribing information for AMITIZA.
AMITIZA (lubiprostone) capsules, for oral use
Initial U.S. Approval: 2006

1 INDICATIONS AND USAGE

Amitiza is a chloride channel activator indicated for the treatment of:

- chronic idiopathic constipation (CIC) in adults. (1.1)
- opioid-induced constipation (OIC) in adult patients with chronic, non-cancer pain, including patients with chronic pain related to prior cancer or its treatment who do not require frequent (e.g., weekly) opioid dosage escalation. (1.2)
  - Limitations of Use:
    Effectiveness of Amitiza in the treatment of OIC in patients taking diphenylheptane opioids (e.g., methadone) has not been established. (1.2, 7.1)
- irritable bowel syndrome with constipation (IBS-C) in women ≥ 18 years old. (1.3)

2 DOSAGE AND ADMINISTRATION

Recommended Dosage (2.1)

- CIC and OIC: 24 mcg twice daily.
- IBS-C: 8 mcg twice daily.
- See full prescribing information for dosage adjustment by indication and degree of hepatic impairment.

Administration Instructions (2.2)

- Swallow capsules whole and do not break apart or chew,
- Take capsules with food and water,
- Assess periodically the need for continuous therapy.

3 DOSAGE FORMS AND STRENGTHS

Capsules: 8 mcg and 24 mcg (3)

4 CONTRAINDICATIONS

Patients with known or suspected mechanical gastrointestinal obstruction. (4, 5.5)

5 WARNINGS AND PRECAUTIONS

- Nausea: Patients may experience nausea; concomitant administration of food may reduce this symptom. (2.2, 5.1)
- Diarrhea: Avoid use in patients with severe diarrhea. Instruct patients to discontinue Amitiza and contact their healthcare provider if severe diarrhea occurs during treatment. (5.2)
- Syncope and Hypotension: May occur after taking the first dose or with subsequent doses. Generally resolves prior to the next dose, but may recur with repeat dosing. Instruct patients to discontinue Amitiza and contact their healthcare provider if symptoms occur. (5.3)
- Dyspnea: May occur within an hour of first dose. Generally resolves within 3 hours, but may recur with repeat dosing. Instruct patients to contact their healthcare provider if symptoms occur. (5.4)
- Bowel Obstruction: Evaluate patients with symptoms suggestive of mechanical gastrointestinal obstruction prior to initiating treatment with Amitiza. (4, 5.5)

6 ADVERSE REACTIONS

Most common adverse reactions (> 4%) are:

- CIC: nausea, diarrhea, headache, abdominal pain, abdominal distension, and flatulence. (6.1)
- OIC: nausea and diarrhea. (6.1)
- IBS-C: nausea, diarrhea, and abdominal pain. (6.1)

To report SUSPECTED ADVERSE REACTIONS, contact Mallinckrodt at 1-800-844-2830 or FDA at 1-800-FDA-1088 or www.fda.gov/medwatch.

8 USE IN SPECIFIC POPULATIONS

- Pregnancy: Based on animal data, may cause fetal harm. (8.1)
- Pediatrics: Safety and effectiveness have not been established in pediatric patients with IBS-C, pediatric functional constipation (PFC), and OIC. (8.4)

FULL PRESCRIBING INFORMATION

1 INDICATIONS AND USAGE

1.1 Chronic Idiopathic Constipation in Adults

Amitiza® is indicated for the treatment of chronic idiopathic constipation (CIC) in adults.

1.2 Opioid-Induced Constipation in Adult Patients with Chronic Non-Cancer Pain

Amitiza is indicated for the treatment of opioid-induced constipation (OIC) in adult patients with chronic non-cancer pain, including patients with chronic pain related to prior cancer or its treatment who do not require frequent (e.g., weekly) opioid dosage escalation.

Limitations of Use:

Effectiveness of Amitiza in the treatment of opioid-induced constipation in patients taking diphenylheptane opioids (e.g., methadone) has not been established. [see Clinical Studies (14.2)]

1.3 Irritable Bowel Syndrome with Constipation

Amitiza is indicated for the treatment of irritable bowel syndrome with constipation (IBS-C) in women at least 18 years old.

2 DOSAGE AND ADMINISTRATION

2.1 Recommended Dosage

The recommended oral dosage of Amitiza by indication and adjustments for patients with moderate (Child Pugh Class B) and severe (Child Pugh Class C) hepatic impairment are shown in Table 1.

Table 1. Recommended Dosage Regimen
 | CIC and OIC | IBS-C
Recommended Adult Dosage Regimen | 24 mcg twice daily | 8 mcg twice daily
Dosage Adjustment for Hepatic Impairment [see Use in Specific Populations (8.6)] | Moderate Impairment (Child-Pugh Class B): 16 mcg twice daily [If the dose is tolerated and an adequate response has not been obtained after an appropriate interval, doses can then be escalated to full dosing with appropriate monitoring of patient response.] | Moderate Impairment (Child-Pugh Class B): No adjustment necessary
Dosage Adjustment for Hepatic Impairment [see Use in Specific Populations (8.6)] | Severe Impairment (Child-Pugh Class C): 8 mcg twice daily | Severe Impairment (Child-Pugh Class C): 8 mcg once daily

2.2 Administration Instructions

- Take Amitiza orally with food and water.
- Swallow capsules whole and do not break apart or chew.
- Physicians and patients should periodically assess the need for continued therapy.

3 DOSAGE FORMS AND STRENGTHS

Amitiza is available as an oval, gelatin capsule containing 8 mcg or 24 mcg of lubiprostone.

- 8 mcg capsules are pink and are printed with "SPI" on one side
- 24 mcg capsules are orange and are printed with "SPI" on one side

4 CONTRAINDICATIONS

Amitiza is contraindicated in patients with known or suspected mechanical gastrointestinal obstruction [see Warnings and Precautions (5.5)].

5 WARNINGS AND PRECAUTIONS

5.1 Nausea

Patients taking Amitiza may experience nausea. Concomitant administration of food with Amitiza may reduce symptoms of nausea [see Adverse Reactions (6.1)].

5.2 Diarrhea

Avoid use of Amitiza in patients with severe diarrhea. Patients should be aware of the possible occurrence of diarrhea during treatment. Instruct patients to discontinue Amitiza and contact their healthcare provider if severe diarrhea occurs [see Adverse Reactions (6.1)].

5.3 Syncope and Hypotension

Syncope and hypotension have been reported with Amitiza in the postmarketing setting and a few of these adverse reactions resulted in hospitalization. Most cases occurred in patients taking 24 mcg twice daily and some occurred within an hour after taking the first dose or subsequent doses of Amitiza. Some patients had concomitant diarrhea or vomiting prior to developing the adverse reaction. Syncope and hypotension generally resolved following Amitiza discontinuation or prior to next dose, but recurrence has been reported with subsequent doses. Several cases reported concomitant use of medications known to lower blood pressure, which may increase the risk for the development of syncope or hypotension.

Patients should be aware of the risk of syncope and hypotension during treatment and that other adverse reactions may increase this risk, such as diarrhea or vomiting.

5.4 Dyspnea

In clinical trials, dyspnea was reported by 3%, 1%, and < 1% of the treated CIC, OIC, and IBS-C populations receiving Amitiza, respectively, compared to 0%, 1%, and < 1% of placebo-treated patients. There have been postmarketing reports of dyspnea when using Amitiza 24 mcg twice daily. Some patients have discontinued treatment because of dyspnea. These events have usually been described as a sensation of chest tightness and difficulty taking in a breath, and generally have an acute onset within 30 to 60 minutes after taking the first dose. They generally resolve within a few hours after taking the dose, but recurrence has been frequently reported with subsequent doses. Instruct patients to contact their healthcare provider if dyspnea occurs.

5.5 Bowel Obstruction

In patients with symptoms suggestive of mechanical gastrointestinal obstruction, perform a thorough evaluation to confirm the absence of an obstruction prior to initiating therapy with Amitiza [see Contraindication (4)].

6 ADVERSE REACTIONS

The following adverse reactions are described below and elsewhere in labeling:

- Nausea [see Warnings and Precautions (5.1)]
- Diarrhea [see Warnings and Precautions (5.2)]
- Syncope and Hypotension [see Warnings and Precautions (5.3)]
- Dyspnea [see Warnings and Precautions (5.4)]

6.1 Clinical Trials Experience

Because clinical studies are conducted under widely varying conditions, adverse reaction rates observed in the clinical studies of a drug cannot be directly compared to rates in the clinical studies of another drug and may not reflect the rates observed in practice.

During clinical development of Amitiza for CIC, OIC, and IBS-C, 1648 patients were treated with Amitiza for 6 months and 710 patients were treated for 1 year (not mutually exclusive).

Chronic Idiopathic Constipation

Adverse reactions in adult dose-finding, efficacy, and long-term clinical studies: The data described below reflect exposure to Amitiza 24 mcg twice daily in 1113 patients with CIC over 3- or 4-week, 6-month, and 12-month treatment periods; and from 316 patients receiving placebo over short-term exposure (≤4 weeks). The placebo population (N = 316) had a mean age of 48 (range 21 to 81) years; was 87% female; 81% Caucasian, 10% African American, 7% Hispanic, 1% Asian, and 12% elderly (≥65 years of age). Of those patients treated with Amitiza 24 mcg twice daily (N=1113), the mean age was 50 (range 19-86) years; 87% were female; 86% Caucasian, 8% African American, 5% Hispanic, 1% Asian, and 17% elderly (≥65 years of age).

The most common adverse reactions (>4%) in CIC were nausea, diarrhea, headache, abdominal pain, abdominal distension, and flatulence.

Table 2 presents data for the adverse reactions that occurred in at least 1% of patients and that occurred more frequently with Amitiza than placebo.

Table 2. Adverse Reactions [Reported in at least 1% of patients treated with Amitiza and greater than placebo] in Clinical Trials of Adults with CIC
System/Adverse Reaction | Placebo | Amitiza 24 mcg Twice Daily
System/Adverse Reaction | N = 316 % | N = 1113 %
Nausea | 3 | 29
Diarrhea | 1 | 12
Headache | 5 | 11
Abdominal pain | 3 | 8
Abdominal distension | 2 | 6
Flatulence | 2 | 6
Vomiting | 0 | 3
Loose stools | 0 | 3
Edema | <1 | 3
Abdominal discomfort [This term combines "abdominal tenderness," "abdominal rigidity," "gastrointestinal discomfort," "stomach discomfort", and "abdominal discomfort."] | 1 | 3
Dizziness | 1 | 3
Chest discomfort/pain | 0 | 2
Dyspnea | 0 | 2
Dyspepsia | <1 | 2
Fatigue | 1 | 2
Dry mouth | <1 | 1

Nausea: Approximately 29% of patients who received Amitiza experienced nausea; 4% of patients had severe nausea and 9% of patients discontinued treatment due to nausea. The rate of nausea was lower among male (8%) and elderly (19%) patients. No patients in the clinical studies were hospitalized due to nausea.

Diarrhea: Approximately 12% of patients who received Amitiza experienced diarrhea; 2% of patients had severe diarrhea and 2% of patients discontinued treatment due to diarrhea.

Electrolytes: No serious adverse reactions of electrolyte imbalance were reported in clinical studies, and no clinically significant changes were seen in serum electrolyte levels in patients receiving Amitiza.

Less common adverse reactions (<1%): fecal incontinence, muscle cramp, defecation urgency, frequent bowel movements, hyperhidrosis, pharyngolaryngeal pain, intestinal functional disorder, anxiety, cold sweat, constipation, cough, dysgeusia, eructation, influenza, joint swelling, myalgia, pain, syncope, tremor, decreased appetite.

Opioid-Induced Constipation

Adverse reactions in adult efficacy and long-term clinical studies: The data described below reflect exposure to Amitiza 24 mcg twice daily in 860 patients with OIC for up to 12 months and from 632 patients receiving placebo twice daily for up to 12 weeks. The total population (N = 1492) had a mean age of 50 (range 20–89) years; was 63% female; 83% Caucasian, 14% African American, 1% American Indian/Alaska Native, 1% Asian; 5% were of Hispanic ethnicity, and 9% were elderly (≥65 years of age).

The most common adverse reactions (>4%) in OIC were nausea and diarrhea.

Table 3 presents data for the adverse reactions that occurred in at least 1% of patients and that occurred more frequently with study drug than placebo.

Table 3. Adverse Reactions [Reported in at least 1% of patients treated with Amitiza and greater than placebo] in Clinical Trials of Adults with OIC
System/Adverse Reaction | Placebo | Amitiza 24 mcg Twice Daily
System/Adverse Reaction | N = 632 % | N = 860 %
Nausea | 5 | 11
Diarrhea | 2 | 8
Abdominal pain | 1 | 4
Flatulence | 3 | 4
Abdominal distension | 2 | 3
Vomiting | 2 | 3
Headache | 1 | 2
Peripheral edema | <1 | 1
Abdominal discomfort [This term combines "abdominal tenderness," "abdominal rigidity," "gastrointestinal discomfort," "stomach discomfort", and "abdominal discomfort."] | 1 | 1

Nausea: Approximately 11% of patients who received Amitiza experienced nausea; 1% of patients had severe nausea and 2% of patients discontinued treatment due to nausea.

Diarrhea: Approximately 8% of patients who received Amitiza experienced diarrhea; 2% of patients had severe diarrhea and 1% of patients discontinued treatment due to diarrhea.

Less common adverse reactions (<1%):fecal incontinence, blood potassium decreased.

Irritable Bowel Syndrome with Constipation

Adverse reactions in adult dose-finding, efficacy, and long-term clinical studies: The data described below reflect exposure to Amitiza 8 mcg twice daily in 1011 patients with IBS-C for up to 12 months and from 435 patients receiving placebo twice daily for up to 16 weeks. The total population (N = 1267) had a mean age of 47 (range 18–85) years; was 92% female; 78% Caucasian, 13% African American, 9% Hispanic, 0.4% Asian, and 8% elderly (≥65 years of age).

The most common adverse reactions (>4%) in IBS-C were nausea, diarrhea, and abdominal pain.

Table 4 presents data for the adverse reactions that occurred in at least 1% of patients and that occurred more frequently with study drug than placebo.

Table 4. Adverse Reactions [Reported in at least 1% of patients treated with Amitiza and greater than placebo] in Clinical Trials of Adults with IBS-C
System/Adverse Reaction | Placebo | Amitiza 8 mcg Twice Daily
System/Adverse Reaction | N = 435 % | N = 1011 %
Nausea | 4 | 8
Diarrhea | 4 | 7
Abdominal pain | 5 | 5
Abdominal distension | 2 | 3

Nausea: Approximately 8% of patients who received Amitiza 8 mcg twice daily experienced nausea; 1% of patients had severe nausea and 1% of patients discontinued treatment due to nausea.

Diarrhea: Approximately 7% of patients who received Amitiza 8 mcg twice daily experienced diarrhea; <1% of patients had severe diarrhea and <1% of patients discontinued treatment due to diarrhea.

Less common adverse reactions (<1%): dyspepsia, loose stools, vomiting, fatigue, dry mouth, edema, increased alanine aminotransferase, increased aspartate aminotransferase, constipation, eructation, gastroesophageal reflux disease, dyspnea, erythema, gastritis, increased weight, palpitations, urinary tract infection, anorexia, anxiety, depression, fecal incontinence, fibromyalgia, hard feces, lethargy, rectal hemorrhage, pollakiuria.

6.2 Postmarketing Experience

The following additional adverse reactions have been identified during post-approval use of Amitiza. Because these reactions are reported voluntarily from a population of uncertain size, it is not always possible to reliably estimate their frequency or establish a causal relationship to drug exposure.

Cardiovascular: syncope and/or hypotension [see Warnings and Precautions (5.3)], tachycardia

Gastrointestinal: ischemic colitis

General: asthenia

Immune System: hypersensitivity reactions including rash, swelling, and throat tightness malaise

Muscoskeletal: muscle cramps or muscle spasms.

7 DRUG INTERACTIONS

7.1 Methadone

Diphenylheptane opioids (e.g., methadone) have been shown in nonclinical studies to dose-dependently reduce the activation of ClC-2 by lubiprostone in the gastrointestinal tract. There is a possibility of a dose-dependent decrease in the efficacy of Amitiza in patients using diphenylheptane opioids. No in vivo interaction studies have been conducted.

The effectiveness of Amitiza in the treatment of OIC in patients taking diphenylhepatane opioids (e.g., methadone) has not been established [see Indications and Usage (1.2)].

8 USE IN SPECIFIC POPULATIONS

8.1 Pregnancy

Risk Summary

Following oral administration, concentrations of lubiprostone in plasma are below the level of quantitation; however, one of the metabolites, M3, has measurable systemic concentrations [see Clinical Pharmacology (12.3)]. Limited available data with lubiprostone use in pregnant women are insufficient to inform a drug associated risk of adverse developmental outcomes. Animal reproduction studies did not show an increase in structural malformations. Although a dose dependent increase in fetal loss was observed in pregnant guinea pigs that received lubiprostone (doses equivalent to 0.2 to 6 times the maximum recommended human dose (MRHD) based on body surface area (mg/m^2)), these effects were probably secondary to maternal toxicity and occurred after the period of organogenesis (see Data).

The background risk of major birth defects and miscarriage for the indicated population is unknown. All pregnancies have a background risk of birth defect, loss, or other adverse outcomes. In the U.S. general population, the estimated background risk of major birth defects and miscarriage in clinically recognized pregnancies is 2 to 4% and 15 to 20%, respectively.

Data

Animal Data

In developmental toxicity studies, pregnant rats and rabbits received oral lubiprostone during organogenesis at doses up to approximately 338 times (rats) and approximately 34 times (rabbits) the maximum recommended human dose (MRHD) based on body surface area (mg/m^2). Maximal animal doses were 2000 mcg/kg/day (rats) and 100 mcg/kg/day (rabbits). In rats, there were increased incidences of early resorptions and soft tissue malformations (situs inversus, cleft palate) at the 2000 mcg/kg/day dose; however, these effects were probably secondary to maternal toxicity. A dose-dependent increase in fetal loss occurred when guinea pigs received lubiprostone after the period of organogenesis, on days 40 to 53 of gestation, at daily oral doses of 1, 10, and 25 mcg/kg/day (approximately 0.2, 2 and 6 times the MRHD based on body surface area (mg/m^2)); however, these effects were probably secondary to maternal toxicity. The potential of lubiprostone to cause fetal loss was also examined in pregnant rhesus monkeys. Monkeys received lubiprostone post-organogenesis on gestation days 110 through 130 at daily oral doses of 10 and 30 mcg/kg/day (approximately 3 and 10 times the MRHD based on body surface area (mg/m^2)). Fetal loss was noted in one monkey from the 10-mcg/kg dose group, which is within normal historical rates for this species. There was no drug-related adverse effect seen in monkeys.

8.2 Lactation

Risk Summary

There are no data available on the presence of lubiprostone in human milk or the effect of lubiprostone on milk production. There are limited data available on the effect of lubiprostone on the breastfed infant. Neither lubiprostone nor its active metabolite (M3) were present in the milk of lactating rats. When a drug is not present in animal milk, it is likely that the drug will not be present in human milk. If present, lubiprostone may cause diarrhea in the breastfed infant (see Clinical Considerations). The developmental and health benefits of breastfeeding should be considered along with the mother's clinical need for Amitiza and any potential adverse effects on the breastfed infant from Amitiza or from the underlying maternal condition.

Clinical Considerations

Infants of nursing mothers being treated with Amitiza should be monitored for diarrhea.

8.4 Pediatric Use

Safety and effectiveness have not been established in pediatric patients with IBS-C, pediatric functional constipation (PFC), and OIC.

Efficacy was not demonstrated for the treatment of PFC in patients 6 years of age and older in a 12 week, randomized, double-blind, placebo-controlled trial conducted in 606 patients 6 to 17 years with PFC comparing Amitiza to placebo. The primary efficacy endpoint was an overall response based on spontaneous bowel movement frequency over the duration of the trial; the treatment difference from placebo was not statistically significant. In this age group, adverse reactions to Amitiza were similar to those reported in adults. In a 36-week, long-term safety extension trial after approximately 9 months of treatment with Amitiza, a single case of reversible elevation of ALT (17-times upper limit of normal [ULN]), AST (13-times ULN), and GGT (9-times [ULN]) was observed in a child with baseline elevated values (less than or equal to 2.5-times ULN).

Juvenile Animal Toxicity Data

In a 13-week oral toxicity study in juvenile rats, a significant decrease in total bone mineral density was observed in female pups at 0.5 mg/kg/day; in male pups, a significantly lower cortical thickness at the tibial diaphysis was observed at 0.5 mg/kg. The 0.5 mg/kg/day dose is approximately 101 times the maximum recommended adult dose of 48 mcg/day, based on body surface area (mg/m^2).

8.5 Geriatric Use

Chronic Idiopathic Constipation

The efficacy of Amitiza 24 mcg twice daily in the elderly (at least 65 years of age) subpopulation with CIC was consistent with the efficacy in the overall study population. Of the total number of patients treated in the dose-finding, efficacy, and long-term studies of Amitiza, 16% were at least 65 years of age, and 4% were at least 75 years of age. Elderly patients taking Amitiza experienced a lower rate of associated nausea compared to the overall study population taking Amitiza (19% vs. 29%, respectively).

Opioid-Induced Constipation

The safety profile of Amitiza in the elderly (at least 65 years of age) subpopulation with OIC (9% were at least 65 years of age and 2% were at least 75 years of age) was consistent with the safety profile in the overall study population. Clinical studies of Amitiza did not include sufficient numbers of patients aged 65 years and over to determine whether they respond differently from younger patients.

Irritable Bowel Syndrome with Constipation

The safety profile of Amitiza in the elderly (at least 65 years of age) subpopulation with IBS-C (8% were at least 65 years of age and 2% were at least 75 years of age) was consistent with the safety profile in the overall study population. Clinical studies of Amitiza did not include sufficient numbers of patients aged 65 years and over to determine whether they respond differently from younger patients.

8.6 Hepatic Impairment

Patients with moderate hepatic impairment (Child-Pugh Class B) and severe hepatic impairment (Child-Pugh Class C) experienced markedly higher systemic exposure of lubiprostone active metabolite M3, when compared to subjects with normal hepatic function [see Clinical Pharmacology (12.3)]. Clinical safety results demonstrated an increased incidence and severity of adverse events in subjects with greater severity of hepatic impairment.

Adjust the dosage of Amitiza in patients with severe hepatic impairment for all indications. Dosage adjustment is also needed for patients with moderate hepatic impairment treated for CIC, and OIC [see Dosage and Administration (2.1)]. No dosing adjustment is required in patients with mild hepatic impairment (Child-Pugh Class A).

10 OVERDOSAGE

There have been six reports of overdosage with Amitiza during clinical development. Of these six cases, only two subjects reported adverse events: one reported vomiting, diarrhea and stomach ache after taking 168 to 192 mcg of Amitiza, and another reported diarrhea and a joint injury on the day of overdose after taking 36 mcg of Amitiza. Adverse reactions that occurred in at least 1% of healthy subjects given a single oral dose of 144 mcg of Amitiza (6 times the highest recommended dose) in a cardiac repolarization study included nausea (45%), diarrhea (35%), vomiting (27%), dizziness (14%), headache (12%), abdominal pain (8%), flushing/hot flash (8%), retching (8%), dyspnea (4%), pallor (4%), stomach discomfort (4%), anorexia (2%), asthenia (2%), chest discomfort (2%), dry mouth (2%), hyperhidrosis (2%), and syncope (2%).

11 DESCRIPTION

Amitiza (lubiprostone) is a chloride channel activator for oral use.

The chemical name for lubiprostone is (–)-7-[(2R,4aR,5R,7aR)-2-(1,1-difluoropentyl)-2-hydroxy-6-oxooctahydrocyclopenta[b]pyran-5-yl]heptanoic acid. The molecular formula of lubiprostone is C20H32F2O5 with a molecular weight of 390.46 and a chemical structure as follows:

Lubiprostone drug substance occurs as white, odorless crystals or crystalline powder, is very soluble in ether and ethanol, and is practically insoluble in hexane and water. Amitiza is available as an imprinted, oval, soft gelatin capsule in two strengths. Pink capsules contain 8 mcg of lubiprostone and the following inactive ingredients: ferric oxide, gelatin, medium-chain triglycerides, purified water, sorbitol, and titanium dioxide. Orange capsules contain 24 mcg of lubiprostone and the following inactive ingredients: D&C Yellow #10, FD&C Red #40, gelatin, medium-chain triglycerides, purified water, and sorbitol.

12 CLINICAL PHARMACOLOGY

12.1 Mechanism of Action

Lubiprostone is a locally acting chloride channel activator that enhances a chloride-rich intestinal fluid secretion without altering sodium and potassium concentrations in the serum. Lubiprostone acts by specifically activating ClC-2, which is a normal constituent of the apical membrane of the human intestine, in a protein kinase A–independent fashion.

By increasing intestinal fluid secretion, lubiprostone increases motility in the intestine, thereby facilitating the passage of stool and alleviating symptoms associated with chronic idiopathic constipation. Patch clamp cell studies in human cell lines have indicated that the majority of the beneficial biological activity of lubiprostone and its metabolites is observed only on the apical (luminal) portion of the gastrointestinal epithelium.

Lubiprostone, via activation of apical ClC-2 channels in intestinal epithelial cells, bypasses the antisecretory action of opiates that results from suppression of secretomotor neuron excitability.

Activation of ClC-2 by lubiprostone has also been shown to stimulate recovery of mucosal barrier function and reduce intestinal permeability via the restoration of tight junction protein complexes in ex vivo studies of ischemic porcine intestine.

12.2 Pharmacodynamics

Although the pharmacologic effects of lubiprostone in humans have not been fully evaluated, animal studies have shown that oral administration of lubiprostone increases chloride ion transport into the intestinal lumen, enhances fluid secretion into the bowels, and improves fecal transit.

12.3 Pharmacokinetics

Following oral administration, concentrations of lubiprostone in plasma are below the level of quantitation (10 pg/mL). Therefore, standard pharmacokinetic parameters such as area under the curve (AUC), maximum concentration (Cmax), and half-life (t½) cannot be reliably calculated. However, the pharmacokinetic parameters of M3 (only measurable active metabolite of lubiprostone) have been characterized.

Absorption

Peak plasma concentrations of M3, after a single oral dose of 24 mcg of lubiprostone, occurred at approximately 1.1 hours. The Cmax was 41.5 pg/mL and the mean AUC0–t was 57.1 pg∙hr/mL. The AUC0–t of M3 increases dose proportionally after single 24-mcg and 144-mcg doses of lubiprostone (6-times the maximum recommended 24 mcg dose).

Food Effect

A study was conducted with a single 72-mcg dose of ^3H-labeled lubiprostone (3-times the maximum recommended 24 mcg dose) to evaluate the potential of a food effect on lubiprostone absorption, metabolism, and excretion. Pharmacokinetic parameters of total radioactivity demonstrated that Cmax decreased by 55% while AUC0–∞ was unchanged when lubiprostone was administered with a high-fat meal. The clinical relevance of the effect of food on the pharmacokinetics of lubiprostone is not clear. However, lubiprostone was administered with food and water in a majority of clinical trials.

Distribution

In vitro protein binding studies indicate lubiprostone is approximately 94% bound to human plasma proteins.

Elimination

Metabolism

Lubiprostone is rapidly and extensively metabolized by 15-position reduction, α-chain β-oxidation, and ω-chain ω-oxidation. In vitro studies using human liver microsomes indicate that cytochrome P450 isoenzymes are not involved in the metabolism of lubiprostone. Further in vitro studies indicate that M3, a metabolite of lubiprostone, is formed by the reduction of the 15-carbonyl moiety to a hydroxy moiety by microsomal carbonyl reductase. M3 makes up less than 10% of the dose of radiolabeled lubiprostone.

Animal studies have shown that metabolism of lubiprostone rapidly occurs within the stomach and jejunum, most likely in the absence of any systemic absorption.

Excretion

Lubiprostone could not be detected in plasma; however, M3 has a t½ ranging from 0.9 to 1.4 hours. After a single oral dose of 72 mcg of ^3H-labeled lubiprostone, 60% of total administered radioactivity was recovered in the urine within 24 hours and 30% of total administered radioactivity was recovered in the feces by 168 hours. Lubiprostone and M3 are only detected in trace amounts in human feces.

Specific Populations

Male and Female Patients

The pharmacokinetics of M3 were similar between male and female subjects.

Patients with Renal Impairment

Sixteen subjects, 34 to 47 years old (8 severe renally impaired subjects [creatinine clearance (CrCl) less than 20 mL/min] who required hemodialysis and 8 control subjects with normal renal function [CrCl above 80 mL/min]), received a single oral 24-mcg dose of Amitiza. Following administration, lubiprostone plasma concentrations were below the limit of quantitation (10 pg/mL). Plasma concentrations of M3 were within the range of exposure from previous clinical experience with Amitiza.

Patients with Hepatic Impairment

Twenty-five subjects, 38 to 78 years old (9 with severe hepatic impairment [Child-Pugh Class C], 8 with moderate impairment [Child-Pugh Class B], and 8 with normal liver function), received either 12 mcg or 24 mcg of Amitiza under fasting conditions. Following administration, lubiprostone plasma concentrations were below the limit of quantitation (10 pg/mL) except for two subjects. In moderately and severely impaired subjects, the Cmax and AUC0–t of the active lubiprostone metabolite M3 were increased, as shown in Table 5.

Table 5. Pharmacokinetic Parameters of the Metabolite M3 for Subjects with Normal or Impaired Liver Function following Dosing with Amitiza
Liver Function Status | Mean (SD) AUC0–t (pg∙hr/mL) | % Change vs. Normal | Mean (SD) Cmax (pg/mL) | % Change vs. Normal
Normal (n=8) | 39.6 (18.7) | n.a. | 37.5 (15.9) | n.a.
Child-Pugh Class B (n=8) | 119 (104) | +119 | 70.9 (43.5) | +66
Child-Pugh Class C (n=8) | 234 (61.6) | +521 | 114 (59.4) | +183

These results demonstrate that there is a correlation between increased exposure of M3 and severity of hepatic impairment. [see Use in Specific Populations (8.6)]

Drug Interaction Studies

Based upon the results of in vitro human microsome studies, there is low likelihood of pharmacokinetic drug–drug interactions with lubiprostone. Additionally, in vitro studies in human liver microsomes demonstrate that lubiprostone does not inhibit cytochrome P450 isoforms 3A4, 2D6, 1A2, 2A6, 2B6, 2C9, 2C19, or 2E1, and in vitro studies of primary cultures of human hepatocytes show no induction of cytochrome P450 isoforms 1A2, 2B6, 2C9, and 3A4 by lubiprostone. Based on the available information, no protein binding–mediated drug interactions of clinical significance are anticipated.

13 NONCLINICAL TOXICOLOGY

13.1 Carcinogenesis, Mutagenesis, Impairment of Fertility

Carcinogenesis

Two 2-year oral (gavage) carcinogenicity studies (one in Crl:B6C3F1 mice and one in Sprague-Dawley rats) were conducted with lubiprostone. In the 2-year carcinogenicity study in mice, lubiprostone doses of 25, 75, 200, and 500 mcg/kg/day (approximately 2, 6, 17, and 42 times the maximum recommended human dose, respectively, based on body surface area (mg/m^2)) were used. In the 2-year rat carcinogenicity study, lubiprostone doses of 20, 100, and 400 mcg/kg/day (approximately 3, 17, and 68 times the maximum recommended human dose, respectively, based on body surface area (mg/m^2)) were used. In the mouse carcinogenicity study, there was no significant increase in any tumor incidences. There was a significant increase in the incidence of interstitial cell adenoma of the testes in male rats at the 400 mcg/kg/day dose. In female rats, treatment with lubiprostone produced hepatocellular adenoma at the 400 mcg/kg/day dose.

Mutagenesis

Lubiprostone was not genotoxic in the in vitro Ames reverse mutation assay, the in vitro mouse lymphoma (L5178Y TK+/−) forward mutation assay, the in vitro Chinese hamster lung (CHL/IU) chromosomal aberration assay, and the in vivo mouse bone marrow micronucleus assay.

Impairment of Fertility

Lubiprostone, at oral doses of up to 1000 mcg/kg/day, had no effect on the fertility and reproductive function of male and female rats. However, the number of implantation sites and live embryos were significantly reduced in rats at the 1000 mcg/kg/day dose as compared to control. The number of dead or resorbed embryos in the 1000 mcg/kg/day group was higher compared to the control group, but was not statistically significant. The 1000 mcg/kg/day dose in rats is approximately 169 times the maximum recommended human dose of 48 mcg/day, based on body surface area (mg/m^2).

14 CLINICAL STUDIES

14.1 Chronic Idiopathic Constipation in Adults

Two double-blinded, placebo-controlled studies of identical design were conducted in patients with CIC. CIC was defined as, on average, less than 3 SBMs per week (a SBM is a bowel movement occurring in the absence of laxative use) along with one or more of the following symptoms of constipation for at least 6 months prior to randomization: 1) very hard stools for at least a quarter of all bowel movements; 2) sensation of incomplete evacuation following at least a quarter of all bowel movements; and 3) straining with defecation at least a quarter of the time.

Following a 2-week baseline/washout period, a total of 479 patients (mean age 47 [range 20 to 81] years; 89% female; 81% Caucasian, 10% African American, 7% Hispanic, 2% Asian, 11% at least 65 years of age) were randomized and received Amitiza 24 mcg twice daily or placebo twice daily for 4 weeks. The primary endpoint of the studies was SBM frequency. The studies demonstrated that patients treated with Amitiza had a higher frequency of SBMs during Week 1 than the placebo patients. In both studies, results similar to those in Week 1 were also observed in Weeks 2, 3, and 4 of therapy (Table 6).

Table 6. Adult Spontaneous Bowel Movement Frequency Rates [Frequency rates are calculated as 7 times (number of SBMs) / (number of days observed for that week).] (Efficacy Studies)
Trial | Study Arm | Baseline Mean ± SD Median | Week 1 Mean ± SD Median | Week 2 Mean ± SD Median | Week 3 Mean ± SD Median | Week 4 Mean ± SD Median | Week 1 Change from Baseline Mean ± SD Median | Week 4 Change from Baseline Mean ± SD Median
Study 1 | Placebo | 1.6 ± 1.3 1.5 | 3.5 ± 2.3 3.0 | 3.2 ± 2.5 3.0 | 2.8 ± 2.2 2.0 | 2.9 ± 2.4 2.3 | 1.9 ± 2.2 1.5 | 1.3 ± 2.5 1.0
Study 1 | Amitiza 24 mcg Twice Daily | 1.4 ± 0.8 1.5 | 5.7 ± 4.4 5.0 | 5.1 ± 4.1 4.0 | 5.3 ± 4.9 5.0 | 5.3 ± 4.7 4.0 | 4.3 ± 4.3 3.5 | 3.9 ± 4.6 3.0
Study 2 | Placebo | 1.5 ± 0.8 1.5 | 4.0 ± 2.7 3.5 | 3.6 ± 2.7 3.0 | 3.4 ± 2.8 3.0 | 3.5 ± 2.9 3.0 | 2.5 ± 2.6 1.5 | 1.9 ± 2.7 1.5
Study 2 | Amitiza 24 mcg Twice Daily | 1.3 ± 0.9 1.5 | 5.9 ± 4.0 5.0 | 5.0 ± 4.2 4.0 | 5.6 ± 4.6 5.0 | 5.4 ± 4.8 4.3 | 4.6 ± 4.1 3.8 | 4.1 ± 4.8 3.0

In both studies, Amitiza demonstrated increases in the percentage of patients who experienced SBMs within the first 24 hours after administration when compared to placebo (57% vs. 37% in Study 1 and 63% vs. 32% in Study 2, respectively). Similarly, the time to first SBM was shorter for patients receiving Amitiza than for those receiving placebo.

Signs and symptoms related to constipation, including abdominal bloating, abdominal discomfort, stool consistency, and straining, as well as constipation severity ratings, were also improved with Amitiza versus placebo. The results were consistent in subpopulation analyses for gender, race, and elderly patients at least 65 years of age.

During a 7-week randomized withdrawal study, patients who received Amitiza during a 4-week treatment period were then randomized to receive either placebo or to continue treatment with Amitiza. In Amitiza-treated patients randomized to placebo, SBM frequency rates returned toward baseline within 1 week and did not result in worsening compared to baseline. Patients who continued on Amitiza maintained their response to therapy over the additional 3 weeks of treatment.

14.2 Opioid-Induced Constipation in Adults with Chronic Non-Cancer Pain

The efficacy of Amitiza in the treatment of OIC in patients receiving opioid therapy for chronic, non-cancer-related pain was assessed in three randomized, double-blinded, placebo-controlled studies. In Study 1, the median age was 52 years (range 20 to 82) and 63% were female. In Study 2, the median age was 50 years (range 21 to 77) and 64% were female. In Study 3, the median age was 50 years (range 21 to 89) and 60% were female. Patients had been receiving stable opioid therapy for at least 30 days prior to screening, which was to continue throughout the 12-week treatment period. At baseline, mean oral morphine equivalent daily doses (MEDDs) were 99 mg and 130 mg for placebo-treated and Amitiza-treated patients, respectively, in Study 1. Baseline mean MEDDs were 237 mg and 265 mg for placebo-treated and Amitiza-treated patients, respectively, in Study 2. In Study 3, baseline mean MEDDs were 330 mg and 373 mg for placebo-treated and Amitiza-treated patients, respectively. The Brief Pain Inventory-Short Form (BPI-SF) questionnaire was administered to patients at baseline and monthly during the treatment period to assess pain control. Patients had documented opioid-induced constipation at baseline, defined as having less than 3 spontaneous bowel movements (SBMs) per week, with at least 25% of SBMs associated with one or more of the following conditions: (1) hard to very hard stool consistency; (2) moderate to very severe straining; and/or (3) having a sensation of incomplete evacuation. Laxative use was discontinued at the beginning of the screening period and throughout the study. With the exception of the 48-hour period prior to first dose and for at least 72 hours (Study 1) or 1 week (Study 2 and Study 3) following first dose, use of rescue medication was allowed in cases where no bowel movement had occurred in a 3-day period. Median weekly SBM frequencies at baseline were 1.5 for placebo patients and 1.0 for Amitiza patients in Study 1 and, for both Study 2 and Study 3, median weekly SBM frequencies at baseline were 1.5 for both treatment groups.

In Study 1, patients receiving non-diphenylheptane (e.g., non-methadone) opioids (n = 431) were randomized to receive placebo (n = 217) or Amitiza 24 mcg twice daily (n = 214) for 12 weeks. The primary efficacy analysis was a comparison of the proportion of "overall responders" in each treatment arm. A patient was considered an "overall responder" if ≥1 SBM improvement over baseline were reported for all treatment weeks for which data were available and ≥3 SBMs/week were reported for at least 9 of 12 treatment weeks. The proportion of patients in Study 1 qualifying as an "overall responder" was 27.1% in the group receiving Amitiza 24 mcg twice daily compared to 18.9% of patients receiving placebo twice daily (treatment difference = 8.2%; p-value = 0.03). Examination of gender and race subgroups did not identify differences in response to Amitiza among these subgroups. There were too few elderly patients (≥ 65 years of age) to adequately assess differences in effects in that population.

In Study 2, patients receiving opioids (N = 418) were randomized to receive placebo (n = 208) or Amitiza 24 mcg twice daily (n = 210) for 12 weeks. Study 2 did not exclude patients receiving diphenylheptane opioids (e.g., methadone). The primary efficacy endpoint was the mean change from baseline in SBM frequency at Week 8; 3.3 vs. 2.4 for Amitiza and placebo-treated patients, respectively; treatment difference = 0.9; p-value = 0.004. The proportion of patients in Study 2 qualifying as an "overall responder," as prespecified in Study 1, was 24% in the group receiving Amitiza compared to 15% of patients receiving placebo. In the subgroup of patients in Study 2 taking diphenylheptane opioids (baseline mean [median] MEDDs of 691 [403] mg and 672 [450] mg for placebo and Amitiza patients, respectively), the proportion of patients qualifying as an "overall responder" was 20.5% (8/39) in the group receiving Amitiza compared to 6.3% (2/32) of patients receiving placebo. Examination of gender and race subgroups did not identify differences in response to Amitiza among these subgroups. There were too few elderly patients (≥ 65 years of age) to adequately assess differences in effects in that population.

In Study 3, patients receiving opioids (N = 451) were randomized to placebo (n = 216) or Amitiza 24 mcg twice daily (n = 235) for 12 weeks. Study 3 did not exclude patients receiving diphenylheptane opioids (e.g., methadone). The primary efficacy endpoint was the change from baseline in SBM frequency at Week 8. The study did not demonstrate a statistically significant improvement in SBM frequency rates at Week 8 (mean change from baseline of 2.7 vs. 2.5 for Amitiza and placebo-treated patients, respectively; treatment difference = 0.2; p-value = 0.76). The proportion of patients in Study 3 qualifying as an "overall responder," as prespecified in Study 1, was 15% in the patients receiving Amitiza compared to 13% of patients receiving placebo. In the subgroup of patients in Study 3 taking diphenylheptane opioids (baseline mean [median] MEDDs of 730 [518] mg and 992 [480] mg for placebo and Amitiza patients, respectively), the proportion of patients qualifying as an "overall responder" was 2% (1/47) in the group receiving Amitiza compared to 12% (5/41) of patients receiving placebo.

14.3 Irritable Bowel Syndrome with Constipation

Two double-blinded, placebo-controlled studies of similar design were conducted in adult patients with IBS-C. IBS was defined as abdominal pain or discomfort occurring over at least 6 months with two or more of the following: 1) relieved with defecation; 2) onset associated with a change in stool frequency; and 3) onset associated with a change in stool form. Patients were sub-typed as having IBS-C if they also experienced two of three of the following: 1) <3 spontaneous bowel movements (SBMs) per week, 2) >25% hard stools, and 3) >25% SBMs associated with straining.

Following a 4-week baseline/washout period, a total of 1154 patients (mean age 47 [range 18 to 85] years; 92% female; 77% Caucasian, 13% African American, 9% Hispanic, 0.4% Asian; 8% at least 65 years of age) were randomized and received Amitiza 8 mcg twice daily (16 mcg/day) or placebo twice daily for 12 weeks. The primary efficacy endpoint was assessed weekly utilizing the patient's response to a global symptom relief question based on a 7-point, balanced scale ("significantly worse" to "significantly relieved"): "How would you rate your relief of IBS symptoms (abdominal discomfort/pain, bowel habits, and other IBS symptoms) over the past week compared to how you felt before you entered the study?"

The primary efficacy analysis was a comparison of the proportion of "overall responders" in each arm. A patient was considered an "overall responder" if the criteria for being designated a "monthly responder" were met in at least 2 of the 3 months on study. A "monthly responder" was defined as a patient who had reported "significantly relieved" for at least 2 weeks of the month or at least "moderately relieved" in all 4 weeks of that month. During each monthly evaluation period, patients reporting "moderately worse" or "significantly worse" relief, an increase in rescue medication use, or those who discontinued due to lack of efficacy, were deemed non-responders.

The percentage of patients in Study 1 qualifying as an "overall responder" was 14% in the group receiving Amitiza 8 mcg twice daily compared to 8% of patients receiving placebo twice daily. In Study 2, 12% of patients in the Amitiza 8 mcg group were "overall responders" versus 6% of patients in the placebo group. In both studies, the treatment differences between the placebo and Amitiza groups were statistically significant.

Results in men: The two randomized, placebo-controlled, double-blinded studies comprised 97 (8%) male patients, which is insufficient to determine whether men with IBS-C respond differently to Amitiza from women.

During a 4-week randomized withdrawal period following Study 1, patients who received Amitiza during the 12-week treatment period were re-randomized to receive either placebo or to continue treatment with Amitiza. In Amitiza-treated patients who were "overall responders" during Study 1 and who were re-randomized to placebo, SBM frequency rates did not result in worsening compared to baseline.

16 HOW SUPPLIED/STORAGE AND HANDLING

Amitiza is available as an oval, soft gelatin capsule containing 8 mcg or 24 mcg of lubiprostone with "SPI" printed on one side. Amitiza is available as follows:

8 mcg pink capsule

- Bottles of 60 (NDC 23635-508-60)

24 mcg orange capsule

- Bottles of 60 (NDC 23635-524-60)

STORAGE AND HANDLING

Store at 25°C (77°F); excursions permitted to 15° to 30°C (59° to 86°F).

Protect from light and extreme temperatures.

17 PATIENT COUNSELING INFORMATION

Administration Instructions

- Instruct patients to take Amitiza orally with food and water to reduce the occurrence of nausea [see Warnings and Precautions (5.1)].
- Swallow capsules whole and do not break apart or chew.
- Physicians and patients should periodically assess the need for continued therapy.

Diarrhea

Inform patients that they may experience diarrhea during treatment with Amitiza. Instruct patients to discontinue Amitiza and contact their healthcare provider if severe diarrhea occurs [see Warnings and Precautions (5.2)].

Syncope and Hypotension

Inform patients that they may experience syncope and hypotension after taking the first dose or subsequent doses of Amitiza. Syncope and hypotension generally resolve prior to the next dose, but may recur with repeat dosing. Instruct patients to discontinue Amitiza and to contact their healthcare provider if these reactions occur [see Warnings and Precautions (5.3)]. Inform patients that other adverse reactions may increase the risk of syncope and hypotension, such as diarrhea or vomiting.

Dyspnea

Inform patients that they may experience dyspnea within an hour of the first dose. Dyspnea generally resolves within 3 hours, but may recur with repeat dosing. Instruct patients to inform their healthcare provider if dyspnea occurs [see Warnings and Precautions (5.4)].

Lactation

Advise lactating women to monitor their human milk-fed infants for diarrhea while taking Amitiza [see Use in Specific Populations (8.2)].

Mallinckrodt and Sucampo, the "M" and "S" brand marks, and the Mallinckrodt Pharmaceuticals and Sucampo logos, are trademarks of a Mallinckrodt or a Sucampo company. © 2024 Mallinckrodt.

For a list of patents, see https://www.mallinckrodt.com/patents/

Marketed by:
Sucampo Pharma Americas LLC (a wholly owned subsidiary of Mallinckrodt Pharmaceuticals)
Bridgewater, NJ 08807, USA
and
SpecGx LLC
Webster Groves, MO 63119, USA

Amitiza is a registered trademark of Sucampo Pharma Americas LLC.

3001

PRINCIPAL DISPLAY PANEL - 8 mcg Capsule Bottle Label

Rx Only

60 Capsules

AMITIZA®
(lubiprostone) capsules
8 mcg

NDC 23635-508-60

SUCAMPO

See package insert for complete prescribing information.
Keep out of reach of children.
Marketed by: Sucampo Pharma Americas LLC, Bridgewater,
NJ 08807, USA and SpecGx LLC, Webster Groves,
MO 63119, USA. Active ingredient made in Japan;
encapsulated in the United States.

Mallinckrodt™

PRINCIPAL DISPLAY PANEL - 24 mcg Capsule Bottle Label

Rx Only

60 Capsules

AMITIZA®
(lubiprostone) capsules
24 mcg

NDC 23635-524-60

SUCAMPO

See package insert for complete prescribing information.
Keep out of reach of children.
Marketed by: Sucampo Pharma Americas LLC, Bridgewater,
NJ 08807, USA and SpecGx LLC, Webster Groves,
MO 63119, USA. Active ingredient made in Japan;
encapsulated in the United States.

Mallinckrodt™